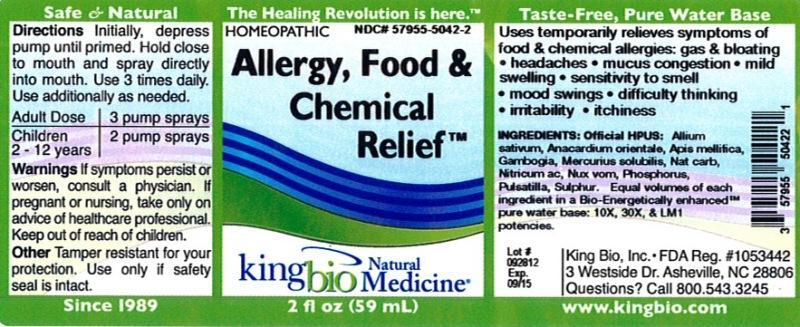 DRUG LABEL: Allergy Food andChemical Relief
NDC: 57955-5042 | Form: LIQUID
Manufacturer: King Bio Inc.
Category: homeopathic | Type: HUMAN OTC DRUG LABEL
Date: 20121011

ACTIVE INGREDIENTS: GARLIC 10 [hp_X]/59 mL; SEMECARPUS ANACARDIUM JUICE 10 [hp_X]/59 mL; APIS MELLIFERA 10 [hp_X]/59 mL; GAMBOGE 10 [hp_X]/59 mL; MERCURIUS SOLUBILIS 10 [hp_X]/59 mL; SODIUM CARBONATE 10 [hp_X]/59 mL; NITRIC ACID 10 [hp_X]/59 mL; STRYCHNOS NUX-VOMICA SEED 10 [hp_X]/59 mL; PHOSPHORUS 10 [hp_X]/59 mL; PULSATILLA VULGARIS 10 [hp_X]/59 mL; SULFUR 10 [hp_X]/59 mL
INACTIVE INGREDIENTS: WATER

Allergy Food and Chemical Relief

Active Ingredients

Official HPUS: Allium sativum, Anacardium orientale, Apis mellifica, Gambogia, Mercurius solubilis, Natrum carbonicum, Nitricum acidum, Nux vomica, Phosphorus, Pulsatilla and Sulphur.

Inactive Ingredient

Equal volumes of each ingredient in a Bio-Energetically enhanced pure water base: 10X, 30X and LM1 potencies.

Purpose

Uses temporarily relieves symptoms of food and chemical allergies:

- gas and bloating
- headaches
- mucus congestion
- mild swelling
- sensitivity to smell
- mood swings
- difficulty thinking
- irritability
- itchiness

Dosage and Administration

Directions: Initially, depress pump until primed. Hold close to mouth and spray one dose directly into mouth. Use additionally as needed.

Adult Dose 3 pump sprays

Children 2-12 years 2 pump sprays

Warnings

If symptoms persist or worsen, or if pregnant or nursing, take only on advice of a healthcare professional. Keep out of reach of children.

Other: Tamper resistant for your protection. Use only if safety seal is intact.

Keep out of reach of children.

Indications and Usage

Uses temporarily relieves symptoms of food and chemical allergies: gas and bloating, headaches, mucus congestion, mild swelling, sensitivity to smell, mood swings, difficulty thinking, irritability, itchiness.

PACKAGE LABEL

King Bio Inc.

3 Westside Drive

Asheville, NC 28806

Questions? Call 800.543.3245

www.kingbio.com